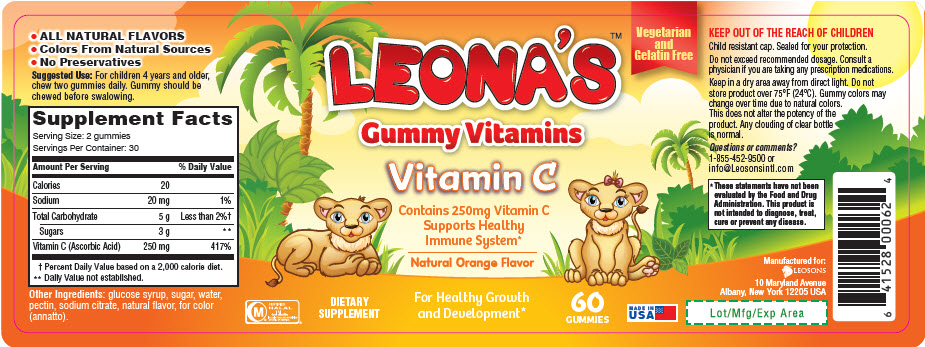 DRUG LABEL: Leonas Vitamin C
NDC: 69626-0062 | Form: TABLET, CHEWABLE
Manufacturer: Leosons Overseas Corp
Category: other | Type: DIETARY SUPPLEMENT
Date: 20180914

ACTIVE INGREDIENTS: ASCORBIC ACID 125 mg/1 1
INACTIVE INGREDIENTS: CORN SYRUP; SUCROSE; WATER; PECTIN; SODIUM CITRATE, UNSPECIFIED FORM; ANNATTO

LEONA'S™ Gummy Vitamins Vitamin C

HEALTH CLAIM

- ALL NATURAL FLAVORS
- Colors From Natural Sources
- No Preservatives

DOSAGE AND ADMINISTRATION

Suggested Use: For children 4 years and older, chew two gummies daily. Gummy should be chewed before swalowing.

STATEMENT OF IDENTITY

Supplement Facts
Serving Size: 2 gummies
Servings Per Container: 30
Amount Per Serving |  | % Daily Value
Calories | 20
Sodium | 20 mg | 1%
Total Carbohydrate | 5 g | Less than 2% [Percent Daily Value based on a 2,000 calorie diet.]
Sugars | 3 g | [Daily Value not established.]
Vitamin C (Ascorbic Acid) | 250 mg | 417%

Other Ingredients: glucose syrup, sugar, water, pectin, sodium citrate, natural flavor, for color (annatto).

WARNINGS

KEEP OUT OF THE REACH OF CHILDREN

Child resistant cap. Sealed for your protection.

Do not exceed recommended dosage. Consult a physician if you are taking any prescription medications.

SAFE HANDLING WARNING

Keep in a dry area away from direct light. Do not store product over 75°F (24°C). Gummy colors may change over time due to natural colors.

This does not alter the potency of the product. Any clouding of clear bottle is normal.

Questions or comments?

1-855-452-9500 or info@Leosonsintl.com

HEALTH CLAIM

*These statements have not been evaluated by the Food and Drug Administration. This product is not intended to diagnose, treat, cure or prevent any disease.

HEALTH CLAIM

CERTIFIED
HALAL
ISLAMIC FOOD AND NUTRITION
COUNCIL OF AMERICA

HEALTH CLAIM

Manufactured for:
LEOSONS
10 Maryland Avenue
Albany, New York 12205 USA

Lot/Mfg/Exp Area

PRINCIPAL DISPLAY PANEL - 60 Vitamin Bottle Label

Vegetarian
and
Gelatin Free

LEONA'S™
Gummy Vitamins
Vitamin C

Contains 250mg Vitamin C
Supports Healthy
Immune System*

Natural Orange Flavor

DIETARY
SUPPLEMENT

For Healthy Growth
and Development*

60
GUMMIES

MADE IN
USA